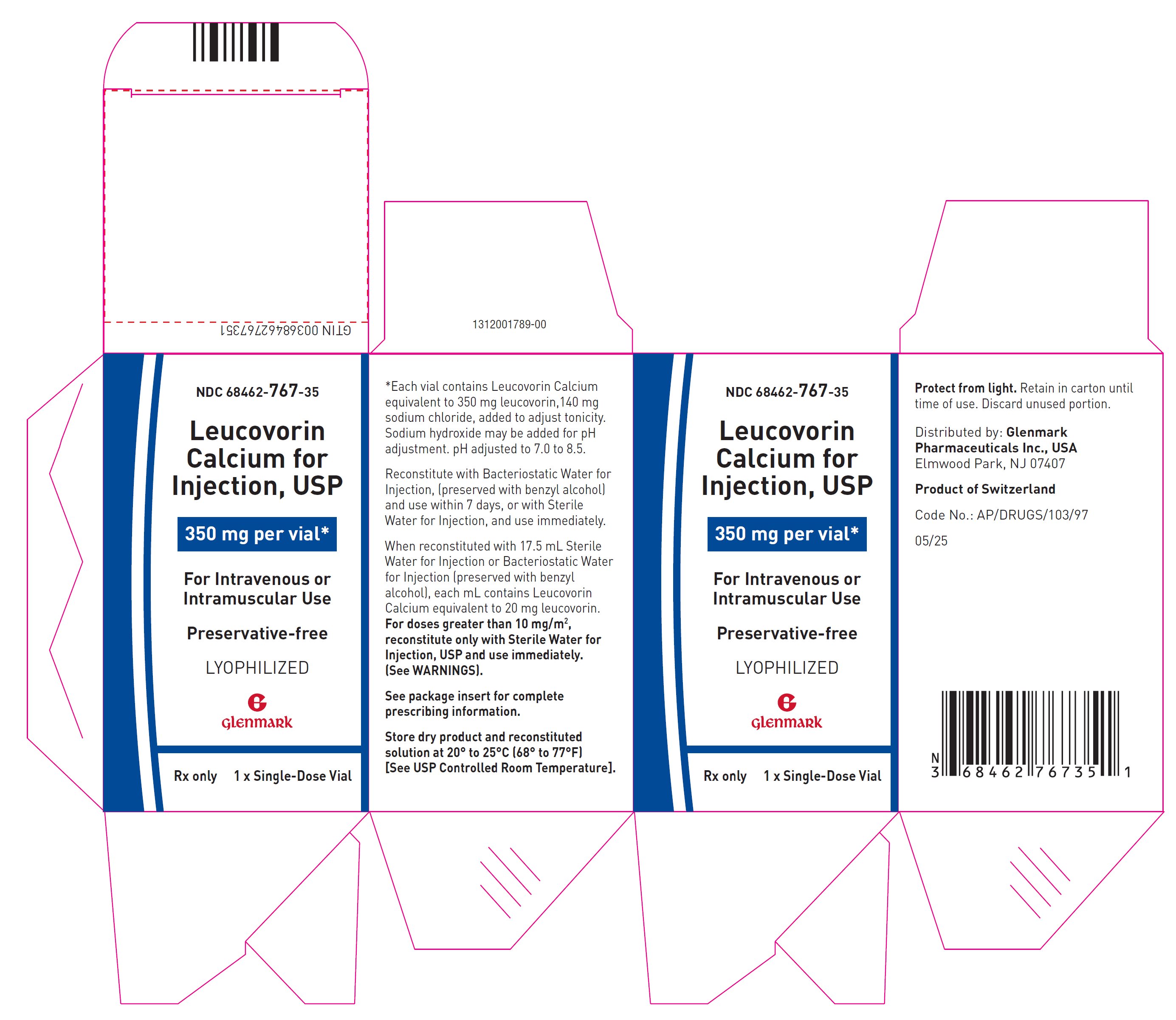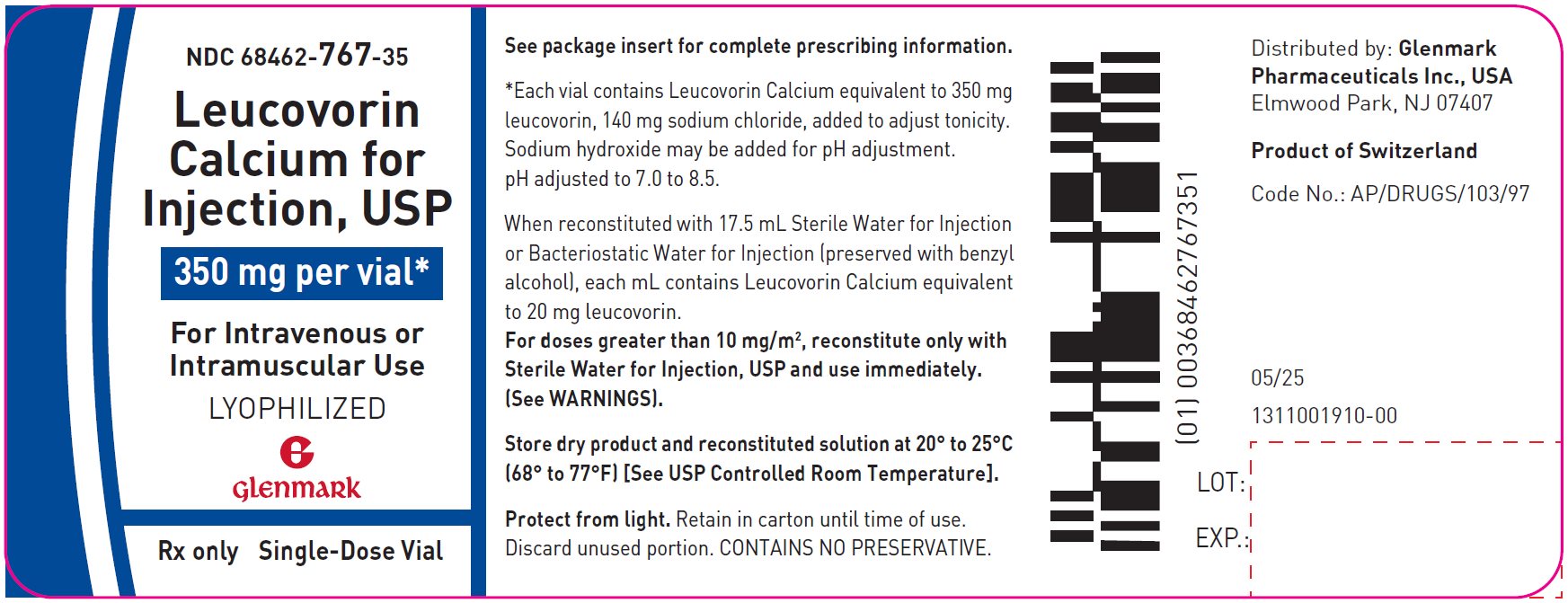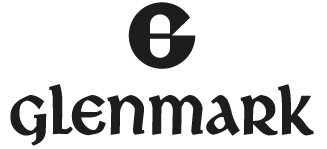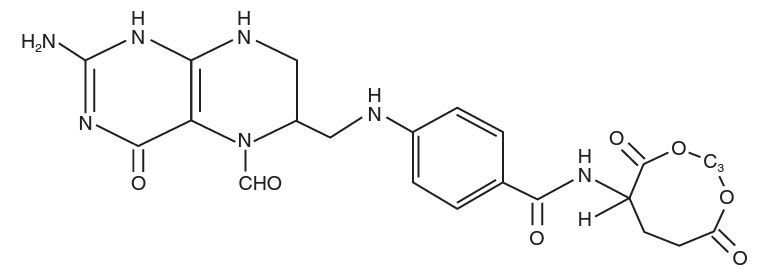 DRUG LABEL: Leucovorin Calcium
NDC: 68462-767 | Form: INJECTION, POWDER, LYOPHILIZED, FOR SOLUTION
Manufacturer: GLENMARK PHARMACEUTICALS INC., USA
Category: prescription | Type: HUMAN PRESCRIPTION DRUG LABEL
Date: 20251209

ACTIVE INGREDIENTS: LEUCOVORIN CALCIUM 350 mg/17.5 mL
INACTIVE INGREDIENTS: SODIUM CHLORIDE; SODIUM HYDROXIDE

Leucovorin Calcium For Injection, USP
Rx Only

DESCRIPTION

Leucovorin is one of several active, chemically reduced derivatives of folic acid. It is useful as an antidote to drugs which act as folic acid antagonists.

Also known as folinic acid, Citrovorum factor, or 5-formyl-5,6,7,8-tetrahydrofolic acid, this compound has the chemical designation of Calcium N-[p-[[[(6RS)-2-amino-5-formyl-5,6,7,8-tetrahydro-4-hydroxy-6-pteridinyl]methyl]amino]benzoyl]-L-glutamate (1:1). The structural formula of leucovorin calcium is:

-

C20H21CaN7O7 M.W.=511.51

Leucovorin Calcium for Injection, USP is a sterile product indicated for intramuscular (IM) or intravenous (IV) administration and is supplied in 350 mg vial.

Each 350 mg vial of Leucovorin Calcium for Injection, USP, when reconstituted with 17.5 mL of sterile diluent, contains leucovorin (as the calcium salt) 20 mg/mL.

In each dosage form, one milligram of leucovorin calcium, USP contains 0.002 mmol of leucovorin and 0.002 mmol of calcium.

This lyophilized product contain no preservative. The inactive ingredient is Sodium Chloride, added to adjust tonicity. Sodium hydroxide may be added for pH adjustment. pH adjusted to 7.0 to 8.5. Reconstitute with Bacteriostatic Water for Injection, which contains benzyl alcohol (see WARNINGS section), or with Sterile Water for Injection.

CLINICAL PHARMACOLOGY

Leucovorin is a mixture of the diastereoisomers of the 5-formyl derivative of tetrahydrofolic acid (THF). The biologically active compound of the mixture is the (-)-l-isomer, known as Citrovorum factor or (-)-folinic acid. Leucovorin does not require reduction by the enzyme dihydrofolate reductase in order to participate in reactions utilizing folates as a source of “one-carbon” moieties. l-Leucovorin (l-5-formyltetrahydrofolate) is rapidly metabolized (via 5, 10-methenyltetrahydrofolate then 5, 10-methylenetetrahydrofolate) to l,5-methyltetrahydrofolate. l,5-Methyltetrahydrofolate can in turn be metabolized via other pathways back to 5,10-methylenetetrahydrofolate, which is converted to 5-methyltetrahydrofolate by an irreversible, enzyme catalyzed reduction using the cofactors FADH2 and NADPH.

Administration of leucovorin can counteract the therapeutic and toxic effects of folic acid antagonists such as methotrexate, which act by inhibiting dihydrofolate reductase.

In contrast, leucovorin can enhance the therapeutic and toxic effects of fluoropyrimidines used in cancer therapy, such as 5-fluorouracil. Concurrent administration of leucovorin does not appear to alter the plasma pharmacokinetics of 5-fluorouracil. 5-Fluorouracil is metabolized to fluorodeoxyuridylic acid, which binds to and inhibits the enzyme thymidylate synthase (an enzyme important in DNA repair and replication).

Leucovorin is readily converted to another reduced folate, 5,10-methylenetetrahydrofolate, which acts to stabilize the binding of fluorodeoxyridylic acid to thymidylate synthase and thereby enhances the inhibition of this enzyme.

The pharmacokinetics after intravenous, intramuscular and oral administration of a 25 mg dose of leucovorin were studied in male volunteers. After intravenous administration, serum total reduced folates (as measured by Lactobacillus casei assay) reached a mean peak of 1259 ng/mL (range 897 to 1625). The mean time to peak was 10 minutes. This initial rise in total reduced folates was primarily due to the parent compound 5-formyl-THF (measured by Streptococcus faecalis assay) which rose to 1206 ng/mL at 10 minutes. A sharp drop in parent compound followed and coincided with the appearance of the active metabolite 5-methyl-THF which became the predominant circulating form of the drug.

The mean peak of 5-methyl-THF was 258 ng/mL and occurred at 1.3 hours. The terminal half-life for total reduced folates was 6.2 hours. The area under the concentration versus time curves (AUCs) for l-leucovorin, d-leucovorin and 5-methyltetrahydrofolate were 28.4 ± 3.5, 956 ± 97 and 129 ± 12 (mg/min/L ± S.E.). When a higher dose of d, l-leucovorin (200 mg/m^2) was used, similar results were obtained. The d-isomer persisted in plasma at concentrations greatly exceeding those of the l-isomer.

After intramuscular injection, the mean peak of serum total reduced folates was 436 ng/mL (range 240 to 725) and occurred at 52 minutes. Similar to IV administration, the initial sharp rise was due to the parent compound. The mean peak of 5-formyl-THF was 360 ng/mL and occurred at 28 minutes. The level of the metabolite 5-methyl-THF increased subsequently over time until at 1.5 hours it represented 50% of the circulating total folates. The mean peak of 5-methyl-THF was 226 ng/mL at 2.8 hours. The terminal half-life of total reduced folates was 6.2 hours. There was no difference of statistical significance between IM and IV administration in the AUC for total reduced folates, 5-formyl-THF, or 5-methyl-THF.

After oral administration of leucovorin reconstituted with aromatic elixir, the mean peak concentration of serum total reduced folates was 393 ng/mL (range 160 to 550). The mean time to peak was 2.3 hours and the terminal half-life was 5.7 hours. The major component was the metabolite 5-methyltetrahydrofolate to which leucovorin is primarily converted in the intestinal mucosa. The mean peak of 5-methyl-THF was 367 ng/mL at 2.4 hours. The peak level of the parent compound was 51 ng/mL at 1.2 hours. The AUC of total reduced folates after oral administration of the 25 mg dose was 92% of the AUC after intravenous administration.

Following oral administration, leucovorin is rapidly absorbed and expands the serum pool of reduced folates. At a dose of 25 mg, almost 100% of the l-isomer but only 20% of the d-isomer is absorbed. Oral absorption of leucovorin is saturable at doses above 25 mg. The apparent bioavailability of leucovorin was 97% for 25 mg, 75% for 50 mg, and 37% for 100 mg.

In a randomized clinical study conducted by the Mayo Clinic and the North Central Cancer Treatment Group (Mayo/NCCTG) in patients with advanced metastatic colorectal cancer three treatment regimens were compared: Leucovorin (LV) 200 mg/m^2 and 5-fluorouracil (5-FU) 370 mg/m^2 versus LV 20 mg/m^2 and 5-FU 425 mg/m^2 versus 5-FU 500 mg/m^2. All drugs were administered by slow intravenous infusion daily for 5 days repeated every 28 to 35 days. Response rates were 26% (p=0.04 versus 5-FU alone), 43% (p=0.001 versus 5-FU alone) and 10% for the high dose leucovorin, low dose leucovorin and 5-FU alone groups respectively. Respective median survival times were 12.2 months (p=0.037), 12 months (p=0.050), and 7.7 months. The low dose LV regimen gave a statistically significant improvement in weight gain of more than 5%, relief of symptoms, and improvement in performance status. The high dose LV regimen gave a statistically significant improvement in performance status and trended toward improvement in weight gain and in relief of symptoms but these were not statistically significant.

In a second Mayo/NCCTG randomized clinical study the 5-FU alone arm was replaced by a regimen of sequentially administered methotrexate (MTX), 5-FU, and LV. Response rates with LV 200 mg/m^2 and 5-FU 370 mg/m^2 versus LV 20 mg/m^2 and 5-FU 425 mg/m^2 versus sequential MTX and 5-FU and LV were respectively 31% (p=<0.01), 42% (p=<0.01), and 14%. Respective median survival times were 12.7 months (p=<0.04), 12.7 months (p=<0.01), and 8.4 months. No statistically significant difference in weight gain of more than 5% or in improvement in performance status was seen between the treatment arms.

The pharmacokinetics of 200 mg doses of leucovorin administered intravenously and orally (reconstituted powder, not tablets) have been evaluated in healthy male subjects. The serum clearance corrected for bioavailability, terminal half-life, and apparent volume of distribution of total folate were not significantly different between routes of administration. The oral bioavailability of the 200 mg dose was 31%. Eighty-three percent of the biologically active IV dose was recovered in the urine within 24 hours, 31% as 5-methyltetrahydrofolate. Twenty percent of the same oral dose was excreted in 24 hours, 16% as 5-methyltetrahydrofolate.

INDICATIONS AND USAGE

Leucovorin Calcium rescue is indicated after high dose methotrexate therapy in osteosarcoma. Leucovorin Calcium is also indicated to diminish the toxicity and counteract the effects of impaired methotrexate elimination and of inadvertent overdosages of folic acid antagonists.

Leucovorin Calcium is indicated in the treatment of megaloblastic anemias due to folic acid deficiency when oral therapy is not feasible.

Leucovorin Calcium is also indicated for use in combination with 5-fluorouracil to prolong survival in the palliative treatment of patients with advanced colorectal cancer. Leucovorin should not be mixed in the same infusion as 5-fluorouracil because a precipitate may form.

CONTRAINDICATIONS

Leucovorin is improper therapy for pernicious anemia and other megaloblastic anemias secondary to the lack of vitamin B12. A hematologic remission may occur while neurologic manifestations continue to progress.

WARNINGS

In the treatment of accidental overdosages of folic acid antagonists, intravenous leucovorin should be administered as promptly as possible. As the time interval between antifolate administration (e.g., methotrexate) and leucovorin rescue increases, leucovorin's effectiveness in counteracting toxicity decreases. In the treatment of accidental overdosages of intrathecally administered folic acid antagonists, do not adminster leucovorin intrathecally. LEUCOVORIN MAY BE HARMFUL OR FATAL IF GIVEN INTRATHECALLY.

Monitoring of the serum methotrexate concentration is essential in determining the optimal dose and duration of treatment with leucovorin.

Delayed methotrexate excretion may be caused by a third space fluid accumulation (i.e., ascites, pleural effusion), renal insufficiency, or inadequate hydration. Under such circumstances, higher doses of leucovorin or prolonged administration may be indicated. Doses higher than those recommended for oral use must be given intravenously.

Because of the benzyl alcohol contained in certain diluents used for reconstituting Leucovorin Calcium for Injection, when doses greater than 10 mg/m^2 are administered, Leucovorin Calcium for Injection should be reconstituted with Sterile Water for Injection, USP, and used immediately (see DOSAGE AND ADMINISTRATION).

Because of the calcium content of the leucovorin solution, no more than 160 mg of leucovorin should be injected intravenously per minute (16 mL of a 10 mg/mL, or 8 mL of a 20 mg/mL solution per minute).

Leucovorin enhances the toxicity of 5-fluorouracil. When these drugs are administered concurrently in the palliative therapy of advanced colorectal cancer, the dosage of 5-fluorouracil must be lower than usually administered. Although the toxicities observed in patients treated with the combination of leucovorin plus 5-fluorouracil are qualitatively similar to those observed in patients treated with 5-fluorouracil alone, gastrointestinal toxicities (particularly stomatitis and diarrhea) are observed more commonly and may be more severe and of prolonged duration in patients treated with the combination.

In the first Mayo/NCCTG controlled trial, toxicity, primarily gastrointestinal, resulted in 7% of patients requiring hospitalization when treated with 5-fluorouracil alone or 5-fluorouracil in combination with 200 mg/m^2 of leucovorin and 20% when treated with 5-fluorouracil in combination with 20 mg/m^2 of leucovorin. In the second Mayo/NCCTG trial, hospitalizations related to treatment toxicity also appeared to occur more often in patients treated with the low dose leucovorin/5-fluorouracil combination than in patients treated with the high dose combination – 11% versus 3%. Therapy with leucovorin and 5-fluorouracil must not be initiated or continued in patients who have symptoms of gastrointestinal toxicity of any severity, until those symptoms have completely resolved. Patients with diarrhea must be monitored with particular care until the diarrhea has resolved, as rapid clinical deterioration leading to death can occur. In an additional study utilizing higher weekly doses of 5-fluorouracil and leucovorin, elderly and/or debilitated patients were found to be at greater risk for severe gastrointestinal toxicity.

Seizures and/or syncope have been reported rarely in cancer patients receiving leucovorin, usually in association with fluoropyrimidine administration, and most commonly in those with CNS metastases or other predisposing factors, however, a causal relationship has not been established.

The concomitant use of leucovorin with trimethoprim-sulfamethoxazole for the acute treatment of Pneumocystis carinii pneumonia in patients with HIV infection was associated with increased rates of treatment failure and morbidity in a placebo- controlled study.

PRECAUTIONS

General

Parenteral administration is preferable to oral dosing if there is a possibility that the patient may vomit and not absorb the leucovorin. Leucovorin has no effect on non-hematologic toxicities of methotrexate such as the nephrotoxicity resulting from drug and/or metabolite precipitation in the kidney.

Since leucovorin enhances the toxicity of fluorouracil, leucovorin/5-fluorouracil combination therapy for advanced colorectal cancer should be administered under the supervision of a physician experienced in the use of antimetabolite cancer chemotherapy. Particular care should be taken in the treatment of elderly or debilitated colorectal cancer patients, as these patients may be at increased risk of severe toxicity.

Laboratory Tests

Patients being treated with the leucovorin/5-fluorouracil combination should have a CBC with differential and platelets prior to each treatment. During the first two courses a CBC with differential and platelets has to be repeated weekly and thereafter once each cycle at the time of anticipated WBC nadir. Electrolytes and liver function tests should be performed prior to each treatment for the first three cycles then prior to every other cycle. Dosage modifications of fluorouracil should be instituted as follows, based on the most severe toxicities:

Diarrhea and/or Stomatitis | WBC/mm^3 Nadir | Platelets/mm^3 Nadir | 5-FU Dose
Moderate | 1,000 to 1,900 | 25 to 75,000 | decrease 20%
Severe | <1,000 | <25,000 | decrease 30%

If no toxicity occurs, the 5-fluorouracil dose may increase 10%. Treatment should be deferred until WBCs are 4,000/mm^3 and platelets 130,000/mm^3. If blood counts do not reach these levels within two weeks, treatment should be discontinued. Patients should be followed up with physical examination prior to each treatment course and appropriate radiological examination as needed. Treatment should be discontinued when there is clear evidence of tumor progression.

Drug Interactions

Folic acid in large amounts may counteract the antiepileptic effect of phenobarbital, phenytoin and primidone, and increase the frequency of seizures in susceptible pediatric patients.

Preliminary animal and human studies have shown that small lquantities of systemically administered leucovorin enter the CSF primarily as 5-methyltetrahydrofolate and, in humans, remain 1 to 3 orders of magnitude lower than the usual methotrexate concentrations following intrathecal administration. However, high doses of leucovorin may reduce the efficacy of intrathecally administered methotrexate.

Leucovorin may enhance the toxicity of 5-fluorouracil (see WARNINGS).

Pregnancy

Teratogenic Effects:

Adequate animal reproduction studies have not been conducted with leucovorin. It is also not known whether leucovorin can cause fetal harm when administered to a pregnant woman or can affect reproduction capacity. Leucovorin should be given to a pregnant woman only if clearly needed.

Nursing Mothers:

It is not known whether this drug is excreted in human milk. Because many drugs are excreted in human milk, caution should be exercised when leucovorin is administered to a nursing mother.

Pediatric Use:

See PRECAUTIONS, Drug Interactions.

Geriatric Use:

Clinical studies of leucovorin calcium did not show differences in safety or effectiveness between subjects over 65 and younger subjects. Other clinical experience has not identified differences in responses between the elderly and younger patients, but greater sensitivity of some older patients cannot be ruled out. This drug is known to be excreted by the kidney and the risk of toxic reactions to the drug may be greater in patients with impaired renal function. Because elder patients are more likely to have decreased renal function, care should be taken in dose selection, and it may be useful to monitor renal function.

ADVERSE REACTIONS

Allergic sensitization, including anaphylactoid reactions and urticaria, has been reported following the administration of both oral and parenteral leucovorin. No other adverse reactions have been attributed to the use of leucovorin per se.

The following table summarizes significant adverse events occurring in 316 patients treated with the leucovorin/5-fluorouracil combinations compared against 70 patients treated with 5-fluorouracil alone for advanced colorectal carcinoma. These data are taken from the Mayo/NCCTG large multicenter prospective trial evaluating the efficacy and safety of the combination regimen.

PERCENTAGE OF PATIENTS TREATED WITH LEUCOVORIN/FLUOROURACIL FOR ADVANCED COLORECTAL CARCINOMA REPORTING ADVERSE EXPERIENCES OR HOSPITALIZED FOR TOXICITY

 | (High LV*) /5-FU (N=155) |  | (Low LV†)/5-FU (N=161) |  | 5-FU Alone (N=70)
 | Any‡ | Grade 3+ § | Any‡ | Grade 3+§ | Any‡ | Grade 3+ §
 | (%) | (%) | (%) | (%) | (%) | (%)
Leukopenia | 69 | 14 | 83 | 23 | 93 | 48
Thrombocytopenia | 8 | 2 | 8 | 1 | 18 | 3
Infection | 8 | 1 | 3 | 1 | 7 | 2
Nausea | 74 | 10 | 80 | 9 | 60 | 6
Vomiting | 46 | 8 | 44 | 9 | 40 | 7
Diarrhea | 66 | 18 | 67 | 14 | 43 | 11
Stomatitis | 75 | 27 | 84 | 29 | 59 | 16
Constipation | 3 | 0 | 4 | 0 | 1 | -
Lethargy/Malaise/Fatigue | 13 | 3 | 12 | 2 | 6 | 3
Alopecia | 42 | 5 | 43 | 6 | 37 | 7
Dermatitis | 21 | 2 | 25 | 1 | 13 | -
Anorexia | 14 | 1 | 22 | 4 | 14 | -
Hospitalization for Toxicity | 5% |  | 15% |  | 7%

* High LV = Leucovorin 200 mg/m^2

† Low LV = Leucovorin 20 mg/m^2

‡ Any = percentage of patients reporting toxicity of any severity

§ Grade 3+ = percentage of patients reporting toxicity of Grade 3 or higher

To report SUSPECTED ADVERSE REACTIONS, contact Glenmark Pharmaceuticals Inc., USA at 1 (888) 721-7115, or the FDA at 1-800-FDA-1088 or www.fda.gov/medwatch.

OVERDOSAGE

Excessive amounts of leucovorin may nullify the chemotherapeutic effect of folic acid antagonists.

DOSAGE AND ADMINISTRATION

Advanced Colorectal Cancer

Either of the following two regimens is recommended:

- 1.Leucovorin is administered at 200 mg/m^2 by slow intravenous injection over a minimum of 3 minutes, followed by 5-fluorouracil at 370 mg/m^2 by intravenous injection.
- 2.Leucovorin is administered at 20 mg/m^2 by intravenous injection followed by 5- fluorouracil at 425 mg/m^2 by intravenous injection.

5-Fluorouracil and leucovorin should be administered separately to avoid the formation of a precipitate.

Treatment is repeated daily for five days. This five-day treatment course may be repeated at 4 week (28-day) intervals, for 2 courses and then repeated at 4 to 5 week (28 to 35 day) intervals provided that the patient has completely recovered from the toxic effects of the prior treatment course.

In subsequent treatment course, the dosage of 5-fluorouracil should be adjusted based on patient tolerance of the prior treatment course. The daily dosage of 5-fluorouracil should be reduced by 20% for patients who experienced moderate hematologic or gastrointestinal toxicity in the prior treatment course, and by 30% for patients who experienced severe toxicity (see PRECAUTIONS: Laboratory Tests). For patients who experienced no toxicity in the prior treatment course, 5-fluorouracil dosages may be increased by 10%. Leucovorin dosages are not adjusted for toxicity.

Leucovorin Rescue After High-Dose Methotrexate Therapy

The recommendations for leucovorin rescue are based on a methotrexate dose of 12 to 15 grams/m^2 administered by intravenous infusion over 4 hours (see methotrexate package insert for full prescribing information).

Leucovorin rescue at a dose of 15 mg (approximately 10 mg/m^2) every 6 hours for 10 doses starts 24 hours after the beginning of the methotrexate infusion. In the presence of gastrointestinal toxicity, nausea or vomiting, leucovorin should be administered parenterally. Do not administer leucovorin intrathecally.

Serum creatinine and methotrexate levels should be determined at least once daily. Leucovorin administration, hydration, and urinary alkalization (pH of 7.0 or greater) should be continued until the methotrexate level is below 5 x 10^-8 M (0.05 micromolar). The leucovorin dose should be adjusted or leucovorin rescue extended based on the following guidelines:

GUIDELINES FOR LEUCOVORIN DOSAGE AND ADMINISTRATION DO NOT ADMINISTER LEUCOVORIN INTRATHECALLY

Clinical Situation |  | Laboratory Findings |  | Leucovorin Dosage and Duration
Normal Methotrexate Elimination |  | Serum methotrexate level approximately 10 micromolar at 24 hours after administration, 1 micromolar at 48 hours, and less than 0.2 micromolar at 72 hours. |  | 15 mg PO, IM, or IV q 6 hours for 60 hours (10 doses starting at 24 hours after start of methotrexate infusion).
Delayed Late Methotrexate Elimination |  | Serum methotrexate level remaining above 0.2 micromolar at 72 hours, and more than 0.05 micromolar at 96 hours after administration. |  | Continue 15 mg PO, IM, or IV q 6 hours, until methotrexate level is less than 0.05 micromolar.
Delayed Early Methotrexate Elimination and/or Evidence of Acute Renal Injury |  | Serum methotrexate level of 50 micromolar or more at 24 hours, or 5 micromolar or more at 48 hours after administration, OR; a 100% or greater increase in serum creatinine level at 24 hours after methotrexate administration (e.g., an increase from 0.5 mg/dL to a level of 1 mg/dL or more). |  | 150 mg IV q 3 hours, until methotrexate level is less than 1 micromolar; then 15 mg IV q 3 hours until methotrexate level is less than 0.05 micromolar.

Patients who experience delayed early methotrexate elimination are likely to develop reversible renal failure. In addition to appropriate leucovorin therapy, these patients require continuing hydration and urinary alkalization, and close monitoring of fluid and electrolyte status, until the serum methotrexate level has fallen to below 0.05 micromolar and the renal failure has resolved.

Some patients will have abnormalities in methotrexate elimination or renal function following methotrexate administration, which are significant but less severe than abnormalities described in the table above. These abnormalities may or may not be associated with significant clinical toxicity. If significant clinical toxicity is observed, leucovorin rescue should be extended for an additional 24 hours (total of 14 doses over 84 hours) in subsequent courses of therapy. The possibility that the patient is taking other medications which interact with methotrexate (e.g., medications which may interfere with methotrexate elimination or binding to serum albumin) should always be reconsidered when laboratory abnormalities or clinical toxicities are observed.

Impaired Methotrexate Elimination or Inadvertent Overdosage

Leucovorin rescue should begin as soon as possible after an inadvertent overdosage and within 24 hours of methotrexate administration when there is delayed excretion (see WARNINGS). Leucovorin 10 mg/m^2 should be administered IV, IM, or PO every 6 hours until the serum methotrexate level is less than 10^-8 M. In the presence of gastrointestinal toxicity, nausea, or vomiting, leucovorin should be administered parenterally. Do not administer leucovorin intrathecally.

Serum creatinine and methotrexate levels should be determined at 24 hour intervals. If the 24 hour serum creatinine has increased 50% over baseline or if the 24 hour methotrexate level is greater than 5 x 10^-6 M or the 48 hour level is greater than 9 x 10^-7 M, the dose of leucovorin should be increased to 100 mg/m^2 IV every 3 hours until the methotrexate level is less than 10^-8 M.

Hydration (3 L/d) and urinary alkalinization with sodium bicarbonate solution should be employed concomitantly. The bicarbonate dose should be adjusted to maintain the urine pH at 7.0 or greater.

Megaloblastic Anemia Due to Folic Acid Deficiency

Up to 1 mg daily. There is no evidence that doses greater than 1 mg/day have greater efficacy than those of 1 mg; additionally, loss of folate in urine becomes roughly logarithmic as the amount administered exceeds 1 mg.

Each 350 mg vial of Leucovorin Calcium for Injection when reconstituted with 17.5 mL of sterile diluent yields a leucovorin concentration of 20 mg per mL. Leucovorin Calcium for Injection contains no preservative. Reconstitute the lyophilized vial product with Bacteriostatic Water for Injection (benzyl alcohol preserved), or Sterile Water for Injection. When reconstituted with Bacteriostatic Water for Injection, the resulting solution must be used within 7 days. If the product is reconstituted with Sterile Water for Injection, use immediately and discard any unused portion.

Because of the benzyl alcohol contained in Bacteriostatic Water for Injection, when doses greater than 10 mg/m^2 are administered, Leucovorin Calcium for Injection should be reconstituted with Sterile Water for Injection, and used immediately. (See WARNINGS.) Because of the calcium content of the leucovorin solution, no more than 160 mg of leucovorin should be injected intravenously per minute (16 mL of a 10 mg/mL, or 8 mL of a 20 mg/mL solution per minute).

Parenteral products should be inspected visually for particulate matter and discoloration prior to administration, whenever solution and container permit.

Leucovorin should not be mixed in the same infusion as 5-fluorouracil, since this may lead to the formation of a precipitate.

HOW SUPPLIED

Leucovorin Calcium for Injection, USP (White to yellow color lyophilized cake or powder) is supplied as a sterile lyophilized powder as follows:

NDC | Leucovorin Calcium for Injection, USP | Package Factor
68462-767-35 | 350 mg Single-Dose Vial | 1 vial per carton

Store at 20° to 25°C (68° to 77°F); excursions permitted to 15° to 30°C (59° to 86°F) [See USP Controlled Room Temperature]. Protect from light. Retain in carton until time of use. Discard unused portion.

For Product Inquiry call 1 (888) 721-7115.

Distributed by:

Glenmark Pharmaceuticals Inc., USA

Elmwood Park, NJ 07407

Revised: May 2025

PACKAGE LABEL.PRINCIPAL DISPLAY PANEL

Container label

NDC 68462-767-35

Rx only

Leucovorin Calcium for Injection, USP

350 mg per vial*

For Intravenous or Intramuscular Use

LYOPHILIZED

Single Dose Vial

Carton label

NDC 68462-767-35

Rx only

Leucovorin Calcium for Injection, USP

350 mg per vial*

For Intravenous or Intramuscular Use

Preservative-free

LYOPHILIZED

1 x Single Dose Vial